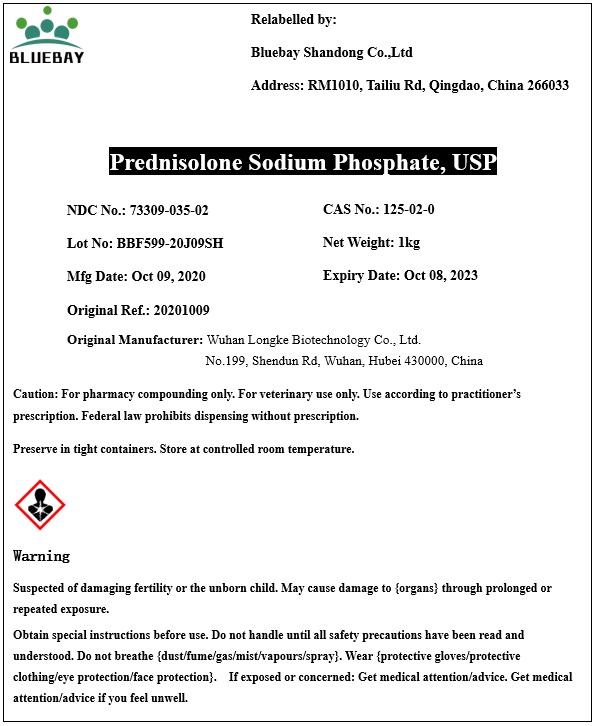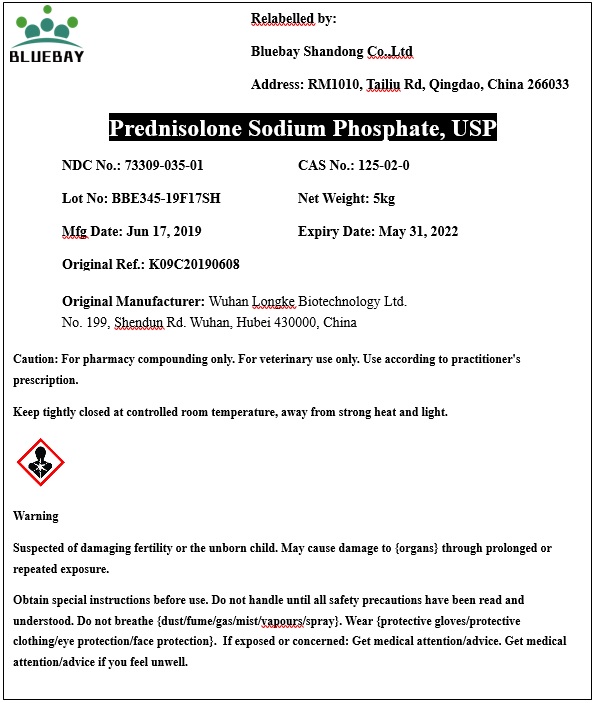 DRUG LABEL: Prednisolone Sodium Phosphate
NDC: 73309-035 | Form: POWDER
Manufacturer: BLUEBAY SHANDONG CO.,LTD
Category: other | Type: BULK INGREDIENT
Date: 20201218

ACTIVE INGREDIENTS: PREDNISOLONE SODIUM PHOSPHATE 1 kg/1 kg

Prednisolone Sodium Phosphate